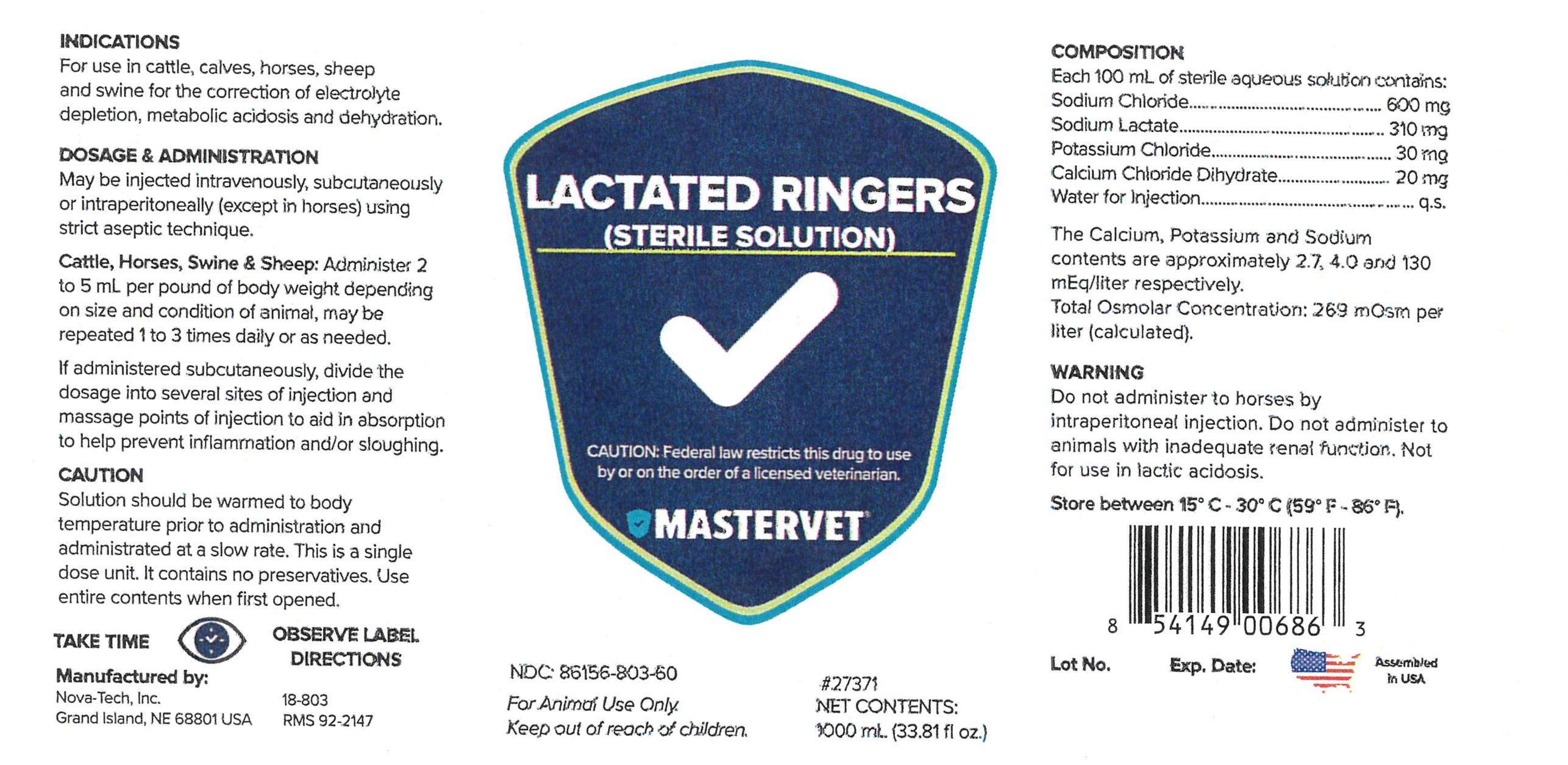 DRUG LABEL: Lactated Ringers
NDC: 86156-803 | Form: INJECTION, SOLUTION
Manufacturer: MasterVet
Category: animal | Type: PRESCRIPTION ANIMAL DRUG LABEL
Date: 20240425

ACTIVE INGREDIENTS: SODIUM CHLORIDE 600 mg/100 mL; SODIUM LACTATE 310 mg/100 mL; POTASSIUM CHLORIDE 30 mg/100 mL; CALCIUM CHLORIDE 20 mg/100 mL

Lactated Ringers

Composition

Each 100 mL of sterile aqueous solution contains:

Sodium Chloride ............................ 600 mg
Sodium Lactate .............................. 310 mg
Potassium Chloride .......................... 30 mg
Calcium Chloride Dihydrate ............... 20 mg
Water for Injection .............................. q.s.

The Calcium, Potassium and Sodium contents are approximately 2.7, 4.0, and 130 mEq/liter respectively. Total Osmolar Concentration: 269 mOsm per liter (calculated).

INDICATIONS

For use in cattle, calves, horses, sheep and swine for the correction of electrolyte depletion, metabolic acidosis and dehydration.

DOSAGE & ADMINISTRATION:

May be injected intravenously, subcutaneously or intraperitoneally (except in horses) using strict aseptic technique.

Cattle, Horses, Swine & Sheep: Administer 2 to 5 mL per pound of body weight depending on size and condition of animal, may be repeated 1 to 3 times daily or as needed.

If administered subcutaneously, divide the dosage into several sites of injection and massage points of injection to aid in absorption to help prevent inflammation and/or sloughing.

CAUTION:

Solution should be warmed to body temperature prior to administration and
administrated at a slow rate. This is a single dose unit. It contains no preservatives. Use entire
contents when first opened.

WARNING:

Do not administer to horses by intraperitoneal injection. Do not administer to
animals with inadequate renal function. Not for use in lactic acidosis.

STORAGE AND HANDLING

Store between 15°C-30°C (59°F-86°F).

WARNINGS AND PRECAUTIONS

TAKE TIME OBSERVE LABEL DIRECTIONS

KEEP OUT OF REACH OF CHILDREN.

VETERINARY INDICATIONS

STERILE SOLUTION

FOR ANIMAL USE ONLY.

CAUTION:

Federal law restricts this drug to use by or on the order of a licensed veterinarian.

INFORMATION FOR OWNERS/CAREGIVERS

Manufactured by:

Nova-Tech, Inc.
Grand Island, NE 68801 USA

18-803

RMS 92-2147

NDC: 86156-803-60

#27371

Net Contents:

1000 mL (33.81 fl oz.)

Lot No.

Exp. Date:

Assembled in USA